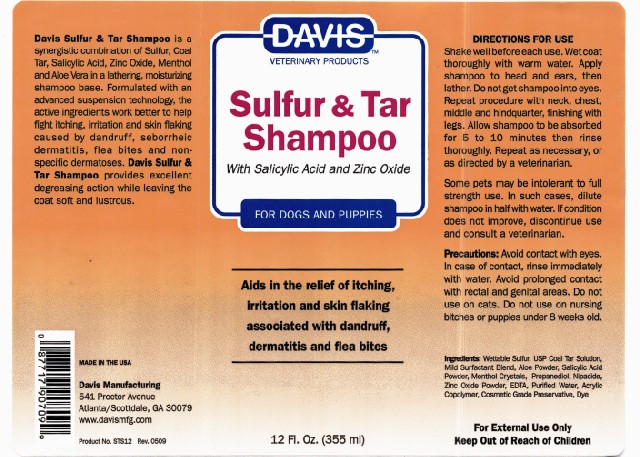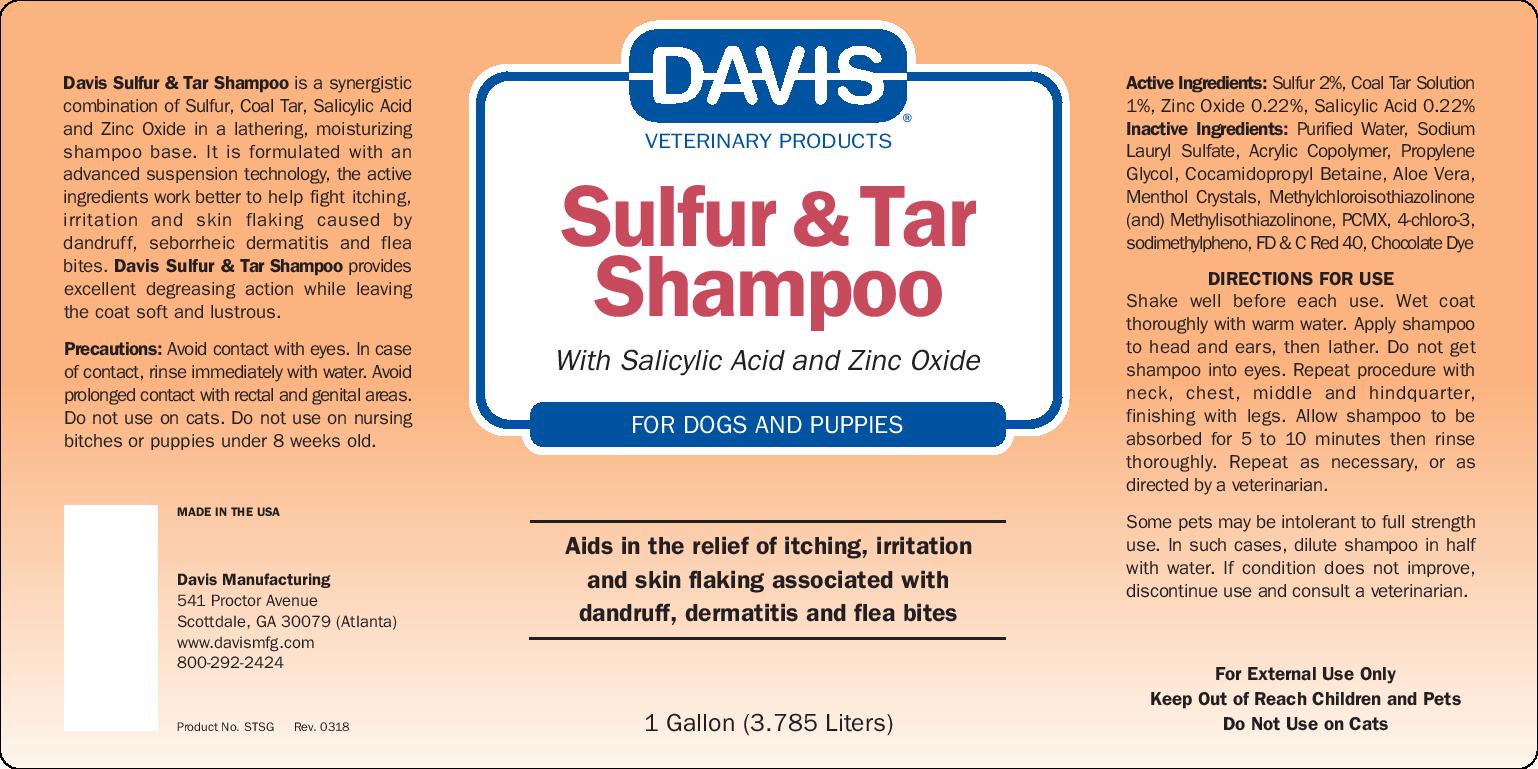 DRUG LABEL: Davis Sulfur and Tar
NDC: 62570-110 | Form: SHAMPOO
Manufacturer: Davis Manufacturing and Packaging Inc
Category: animal | Type: OTC ANIMAL DRUG LABEL
Date: 20180628

ACTIVE INGREDIENTS: SULFUR 20 mg/1 g; COAL TAR 10 mg/1 g; ZINC OXIDE 2.2 mg/1 g; SALICYLIC ACID 2.2 mg/1 g
INACTIVE INGREDIENTS: WATER; SODIUM LAURYL SULFATE; METHACRYLIC ACID - ETHYL ACRYLATE COPOLYMER (1:1) TYPE A; PROPYLENE GLYCOL; COCAMIDOPROPYL BETAINE; Chloroxylenol; ALOE VERA LEAF; METHYLCHLOROISOTHIAZOLINONE/METHYLISOTHIAZOLINONE MIXTURE; FD&C RED NO. 40; MENTHOL

Davis Sulfur & Tar Shampoo

DESCRIPTION

Davis Sulfur & Tar Shampoo is a synergistic combonation of Sulfur, Coal Tar, Salicylic Acid, Zinc Oxide, in a lathering shampoo base. It is formulated with an advanced suspension technology, the active ingredients work better to help fight itching, irritation, and skin flaking caused by dandruff, seborrheic dermititis and flea bites. Davis Sulfur & Tar provides excellent degreasing action while leaving the coat soft and lustrous.

PRECAUTIONS

Precautions: Avoid contact with eyes. In case of contact, rinse immediatly with water. Avoid prolonged contact with rectam and genital areas. DO not use on cats. Do not use on nursing bitches or puppies under 8 weeks old.

MADE IN THE USA

Davis Manufacturing

541 Proctor Avenue

Scottdale, GA (Atlanta)

www.davismfg.com

800-292-2424

Product No. STSG Rev. 0318

ACTIVE INGREDIENT

Active Ingredients: Sulfur 2%, Coal Tar Solution 1%, Zinc Oxide 0.22%, Salicylic Acid 0.22%

INACTIVE INGREDIENT

Inactive Ingredients: Purified Water, Sodium Lauryl Sulfate, Acrylic Copolymer, Propylene Glycol, Cocamidopropyl Betanie, Aloe Vera, Menthol Crystals, Methylchloroisothiazolinone (and) Methylisothiazolinone, FD&C Red 30, Chocolate Dye

DIRECTIONS FOR USE

Shake well before each use. Wet coat thoroughly with warm water. Apply shampoo to head and ears, then lather. Do not get shampoo into eyes. Repeat procedure with neck, chest, middle and hindquarter, finishing with legs. Allow shampoo to be absorbed for 5 to 10 minutes then rinse thoroughly. Repeat as necessary, or as directed by a vereninarian.

GENERAL PRECAUTIONS

Some pets may be intolerant to full strength use. In such cases, dilute shampoo in half with water. If condition does not improve, discontinue use and consult a veterinarian.

KEEP OUT OF REACH OF CHILDREN

For External Use Only

Keep Out of Reach of Chlidren and Pets

Do Not Use on Cats

Sulfur & Tar Gallon

DAVIS VETERINARY PRODUCTS

Sulfur & Tar

Shampoo

With Salicylic Acid and Zinc Oxide

FOR DOGS AND PUPPIES

Aids in the relief of itching, irritation and skin flaking associated with dandruff, dermititis and flea bites

1 Gallon (3.785 Liters)

Sulfur & Tar 12oz

DAVIS VETERINARY PRODUCTS

Sulfur & Tar

Shampoo

With Salicylic Acid and Zinc Oxide

FOR DOGS AND PUPPIES

Aids in the relief of itching, irritation and skin flaking associated with dandruff, dermititis and flea bites

1 Gallon (3.785 Liters)

12 Fl. Oz. (355 ml)